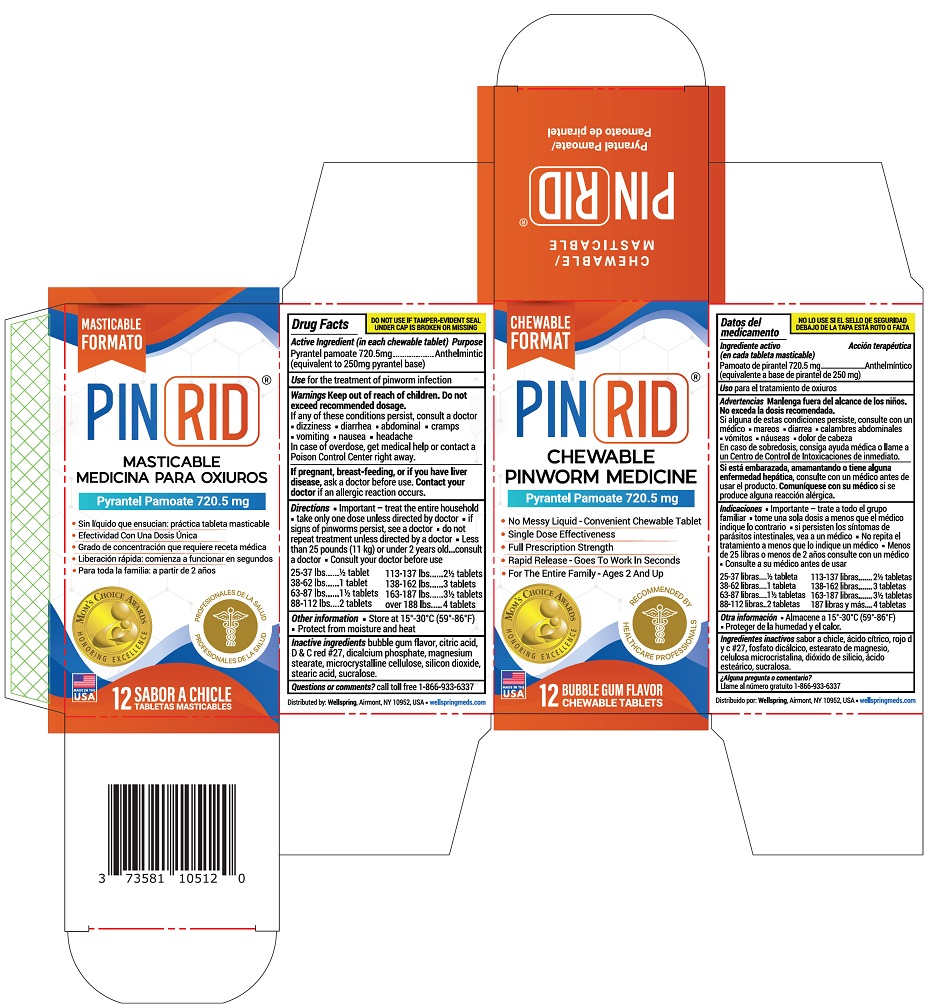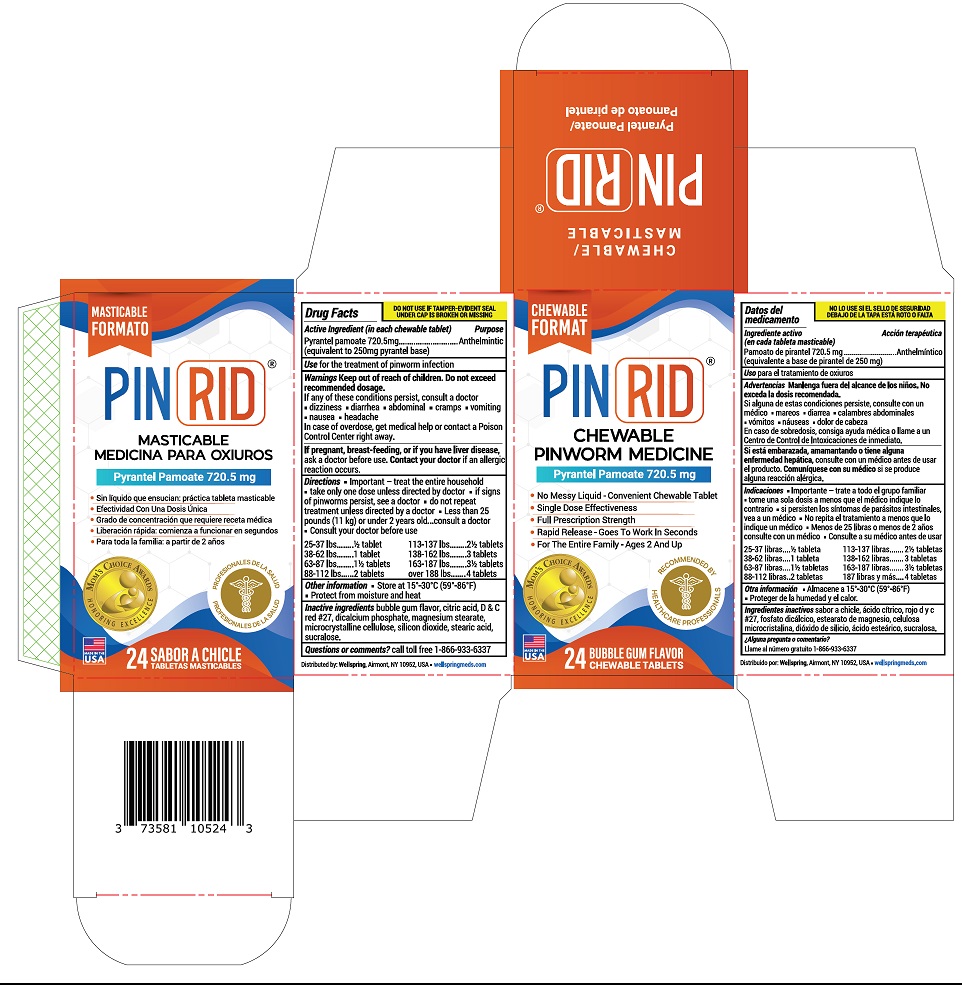 DRUG LABEL: PINRID
NDC: 73581-111 | Form: TABLET
Manufacturer: YYBA CORP
Category: otc | Type: HUMAN OTC DRUG LABEL
Date: 20250702

ACTIVE INGREDIENTS: PYRANTEL PAMOATE 250 mg/1 1
INACTIVE INGREDIENTS: CITRIC ACID MONOHYDRATE; D&C RED NO. 27; ANHYDROUS DIBASIC CALCIUM PHOSPHATE; MAGNESIUM STEARATE; MICROCRYSTALLINE CELLULOSE; SILICON DIOXIDE; STEARIC ACID; SUCRALOSE

PINRID

Drug Facts

Active Ingredient (in each chewable tablet)

Pyrantel pamoate 720.5 mg

(equivalent to 250 mg pyrantel base)

Purpose

Anthelmintic

Use

for the treatment of pinworm infection

Warnings

Keep out of reach of children. Do not exceed recommended dosage.

ASK DOCTOR

If any of these conditions persist, consult a doctor

• dizziness
• diarhea
• abdominal cramps
• vomiting
• nausea
• headache

In case of overdose, get medical help or contact a poison control center rightaway.

PREGNANCY OR BREAST FEEDING

If pregnant, breast-feeding, or if you have liver disease, ask a doctor before use. Contact your doctorif an allergic reaction occurs.

Directions

- Important- treat the entire household
- take only one dose unless directed by doctor
- if signs of pinworms persist, see a doctor
- do not repeat treatment unless directed by a doctor
- less than 25 pounds (11 kg) or under 2 years old, consult a doctor
- Consult your doctor before use

25-37 lb | ½ tablet
38-62 lbs | 1 tablets
63-87 lbs | 1½ tablets
88-112 lbs | 2 tablets
113-137 lbs | 2½ tablets
138-162 lbs | 3 tablets
163-187 lbs | 3½ tablets
over 188 lbs | 4 tablets

Other information:

- Store at 15°-30°C (59° - 86 °F)
- Protect from moisture and heat

Intactive ingredients

bubble gum flavor, citric acid, D&C red#27, dicalcium phosphate, magnesium stearate, microcrystalline cellulose, silicon dioxide, stearic acid, sucralose.

Questions or comments:

call toll free 1-866-933-6337